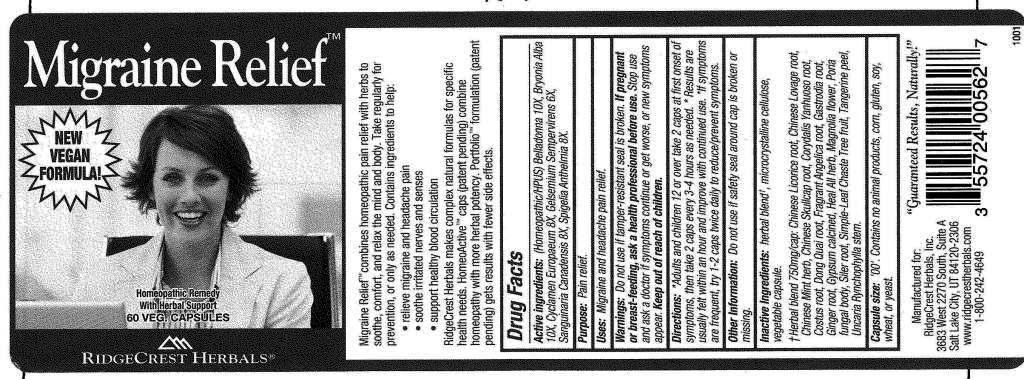 DRUG LABEL: Migraine Relief
NDC: 57520-0423 | Form: CAPSULE
Manufacturer: Apotheca Company
Category: homeopathic | Type: HUMAN OTC DRUG LABEL
Date: 20110628

ACTIVE INGREDIENTS: ATROPA BELLADONNA 10 [hp_X]/1 1; BRYONIA ALBA ROOT 10 [hp_X]/1 1; CYCLAMEN PURPURASCENS TUBER 8 [hp_X]/1 1; GELSEMIUM SEMPERVIRENS ROOT 6 [hp_X]/1 1; SANGUINARIA CANADENSIS ROOT 8 [hp_X]/1 1; SPIGELIA ANTHELMIA 8 [hp_X]/1 1
INACTIVE INGREDIENTS: GLYCYRRHIZA URALENSIS; LIGUSTICUM SINENSE ROOT; MENTHA ARVENSIS FLOWERING TOP; SCUTELLARIA BAICALENSIS ROOT; CORYDALIS YANHUSUO TUBER; COSTUS ROOT OIL; ANGELICA SINENSIS ROOT; ANGELICA DAHURICA ROOT; GASTRODIA ELATA TUBER; GINGER; PRUNELLA VULGARIS FLOWERING TOP; MAGNOLIA OFFICINALIS FLOWER; CELLULOSE, MICROCRYSTALLINE; FU LING; SAPOSHNIKOVIA DIVARICATA ROOT; VITEX TRIFOLIA FRUIT; TANGERINE PEEL; UNCARIA RHYNCHOPHYLLA STEM; CALCIUM SULFATE HEMIHYDRATE

Migraine Relief

ACTIVE INGREDIENT

ACTIVE INGREDIENTS: Belladonna 10X, Bryonia 10X, Cyclamen europaeum 8X, Gelsemium sempervirens 6X, Sanguinaria canadensis 8X, Spigelia anthelmia 8X.

PURPOSE

USES: Migraine Headache pain relief

WARNINGS:

If pregnant or breast-feeding, ask a health professional before use.

Stop use and ask a doctor if symptoms continue or get worse, or new symptoms appear

Keep our of reach of children. In case of overdose, get medical help or contact a Poison Control Center right away.

Do not use if safety seal around cap is broken or missing.

DOSAGE AND ADMINISTRATION

DIRECTIONS: Adults and children 12 or over take 2 caps at first onset of symptoms, then take 2 caps every 3-4 hours as needed. Results are usually felt within an hour and improve with continued use. If symptoms are frequent, try 1-2 caps twice daily to reduce/prevent symptoms.

INACTIVE INGREDIENT

INACTIVE INGREDIENTS: Microcrystalline cellulose, Vegetable capsule (cellulose). Herbal blend - Chinese licorice root, Chinese lovage root, Chinese mint herb, Chinese skullcap root, Corydalis yanhusuo root, Costus root, Dong quai root, Fragrant angelica root, Gastrodia root, Ginger root, Gypsum calcined, Heal all herb, Magnolia flower, Poria fungal body, Siler root, Simple-leaf chaste tree fruit, Tangerine peel, Uncaria rhynchophylla stem.

Capsule Size: '00'. Contains no animal products, corn, gluten, soy, wheat, or yeast.

KEEP OUT OF REACH OF CHILDREN. In case of overdose, get medical help or contact a Poison Control Center right away.

INDICATIONS AND USAGE

USES: Migraine Headache pain

QUESTIONS

Manufactured for:

RidgeCrest Herbals, Inc.

3683 West 2270 South, Suite A

Salt Lake City, UT 84120-2306

www.ridgecrestherbals.com

1-800-242-4649

PACKAGE LABEL

Migraine Relief

NEW VEGAN FORMULA

Homeopathic Remedy With Herbal Support

RIDGECREST HERBALS

60 VEG CAPSULES